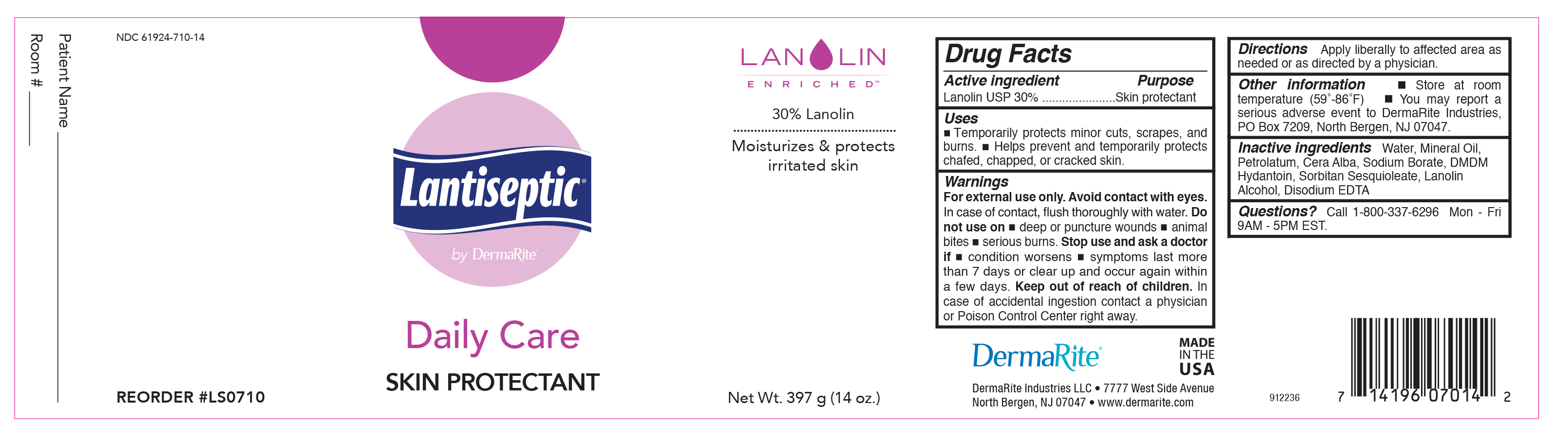 DRUG LABEL: Lantiseptic Dry Skin Therapy
NDC: 61924-710 | Form: CREAM
Manufacturer: Dermarite Industries LLC
Category: otc | Type: HUMAN OTC DRUG LABEL
Date: 20241205

ACTIVE INGREDIENTS: LANOLIN 300 mg/1 g
INACTIVE INGREDIENTS: YELLOW WAX; EDETATE DISODIUM; LANOLIN ALCOHOLS; MINERAL OIL; PETROLATUM; WATER; SODIUM BORATE; SORBITAN SESQUIOLEATE

Lantiseptic by Dermarite Daily Care Skin Protectant

Active Ingredient

Lanolin USP 30%

Purpose

Skin Protectant

Uses

- Temporarily protects minor cuts, scrapes, and burns
- Helps prevent and temporarily protects chafed, chapped, or cracked skin.

Warnings

• For external use only. • Avoid contact with eyes. •In case of contact, flush thoroughly with water.

Do not use on

- deep or puncture wounds
- animal bites
- serious burns

Stop use and ask a doctor if

- conditions worsen
- symptoms last more than 7 days or clear up and occur again within a few days.

Keep our of reach of children

In case of accidental ingestion contact a physician or Poison Control Center right away.

Directions

Apply liberally to affected area as needed or as directed by a physician.

Other Information

- Store at room temperature (59-86°F)
- You may report a serious adverse event to DermaRite Industries, PO Box 7209, North Bergen, NJ07047

Inactive Ingredients

Water, Mineral Oil, Petrolatum, Cera Alba, Sodium Borate, DMDM Hydantoin, Sorbitan Sesquioleate, Lanolin Alcohol, Disodium EDTA

Questions or Comments?

Call 1-800-337-6296 Mon-Fri 9AM-5PM EST.